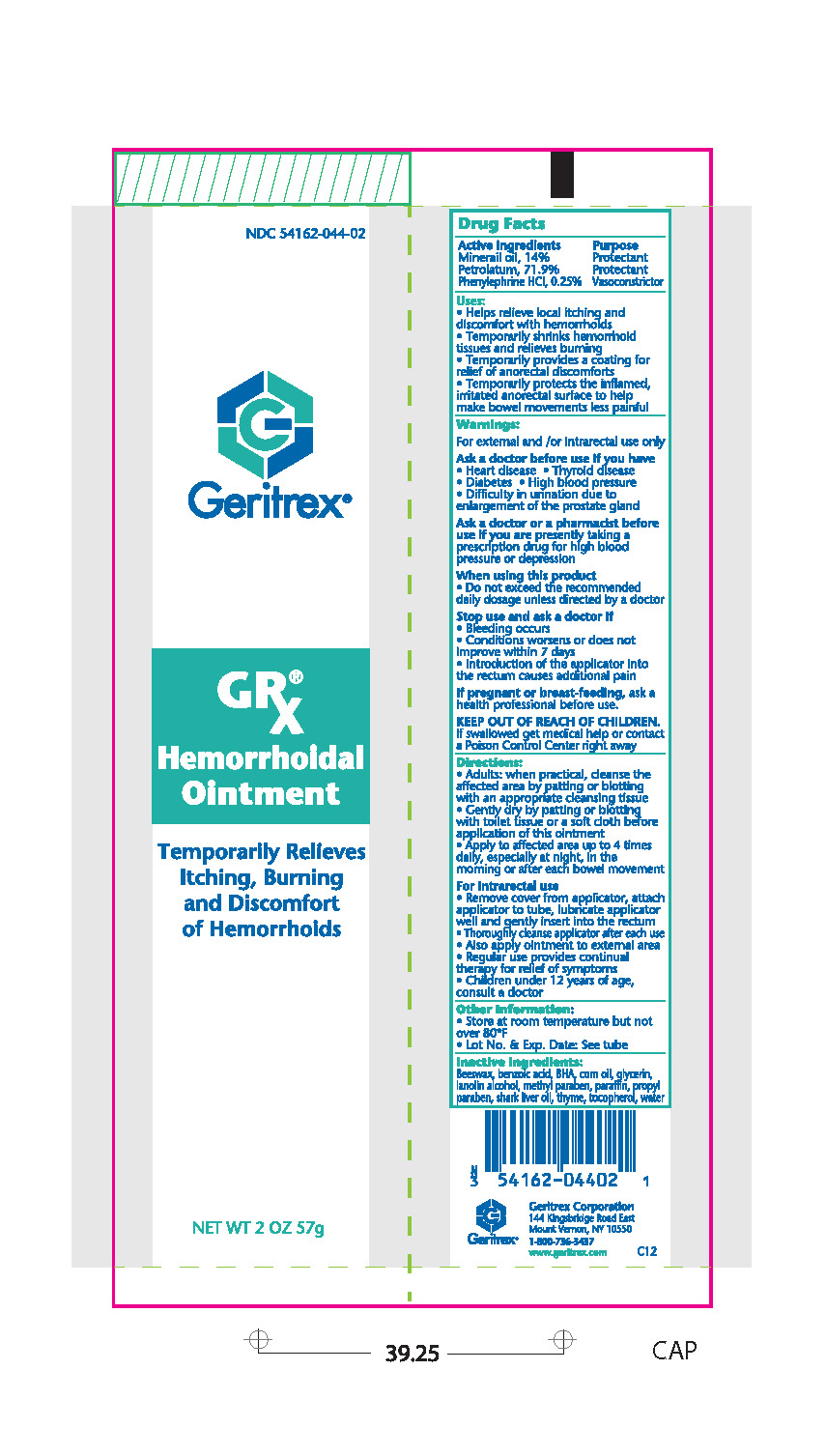 DRUG LABEL: Hemorrhoidal
NDC: 54162-044 | Form: OINTMENT
Manufacturer: Geritrex LLC
Category: otc | Type: HUMAN OTC DRUG LABEL
Date: 20150731

ACTIVE INGREDIENTS: MINERAL OIL 7.98 g/57 g; PETROLATUM 40.983 g/57 g; PHENYLEPHRINE HYDROCHLORIDE 0.1425 g/57 g
INACTIVE INGREDIENTS: YELLOW WAX; BENZOIC ACID; BUTYLATED HYDROXYANISOLE; CORN OIL; GLYCERIN; LANOLIN ALCOHOLS; METHYLPARABEN; PARAFFIN; PROPYLPARABEN; SHARK LIVER OIL; THYME; TOCOPHEROL

Hemorrhoidal Ointment

Uses:

- Helps relieve local itching and discomfort with hemorrhoids.
- Temporarily shrinks hemorrhoid tissues and relieves burning.
- Temporarily provides a coating for relief of anorectal discomforts
- Temporarily protects the inflamed, irritated anorectal surface to hlep make bowel movements less painful

Warnings:

For external and/or intrarectal use only

Ask a doctor before use if you have

- Heart disease
- Thyroid disease
- Diabetes
- High Blood pressure
- Difficulty in urination due to enlargement of the prostate gland

Ask a doctor or a pharmacist before use if you are presently taking a prescription drug for high blood pressure or depression.

When using this product:

Do not exceed the recommended daily dosage unless directed by a doctor

Stop use and ask a doctor if:

- Bleeding occurs
- Condition worsens or does not improve within 7 days
- Introduction of the applicator into the rectum causes additional pain

Directions:

- Adults: when practical, cleanse the affected area by patting or blotting with an appropriate cleansing tissue.
- Gently dry by patting or blotting with toilet tissue or a soft cloth before application of this ointment
- Apply to affected area up to 4 times daily, especially at night, in the morning or after each bowel movement.

For Intrarectal use

- Remove cover from applicator, attach applicator to tube, lubricate applicator well and gently insert into the rectum.
- Thoroughly cleanse applicator after each use
- Also apply ointment to external area
- Regular use provides continual therapy for relief of symptoms
- Children under 12 years of age, consult a doctor

Other Information:

Store at room temperature but not over 80° F
Lot No. & Exp Date: See tube

Inactive Ingredients:

Beeswax, benzoic acid, BHA, corn oil, glycern, lanolin alcohol, methyparaben, paraffin, propylparaben, shark liver oil, thyme, tocopherol, water.